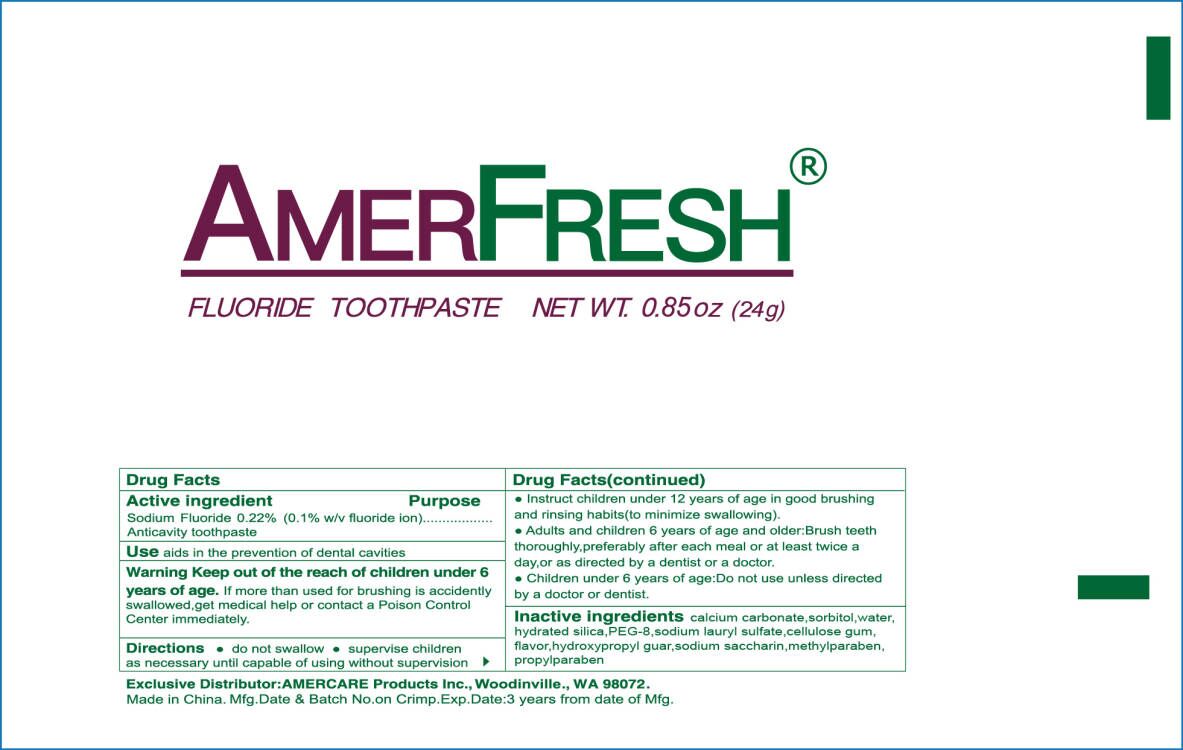 DRUG LABEL: AMERFRESH FLUORIDE
NDC: 85162-002 | Form: PASTE, DENTIFRICE
Manufacturer: Yangzhou ONE & ONLY Personal Care Products Co., LTD
Category: otc | Type: HUMAN OTC DRUG LABEL
Date: 20250116

ACTIVE INGREDIENTS: SODIUM FLUORIDE 0.1 g/100 g
INACTIVE INGREDIENTS: SACCHARIN SODIUM; SORBITOL; SODIUM CARBONATE; HYDRATED SILICA; SODIUM LAURYL SULFATE; WATER; HYDROXYPROPYL GUAR (2500-4500 MPA.S AT 1%); METHYLPARABEN; PROPYLPARABEN

86152-002

Active ingredients

Sodium Fluoride 0.22%(0.1 w/v Fluoride ion)

Purpose

anticavity toothpaste

Uses

Aids in the prevention of dental cavities.

Warnings

Keep out of the reach of children under 6 years of age. If more than used for brushing is accidently swallowed,get medical help or contact a Poison Control Center immediately.

Keep out of reach of children.

Directions

- do not swallow
- supervise children as necessary until capable of useing without supervision
- instruct children under 12 years of age in good brushing and rinsing habits(to minimize swallowing).
- Adults and children 6 years of age and older:Brush teeth thoroughly,preferably after each meal or at least twice a day,or as directed by a dentist or a physician.
- Children under 6 years of age:do not use unless directed by a doctor or dentist.

INACTIVE INGREDIENT

Calcium Carbonate, Sorbitol, Hydrated Silica, Water, PEG-8, Sodium Lauryl Sulfate, Cellulose Gum, Flavor, Hydroypropyl Guar, Sodium Saccharin, Methylparaben, Propylparaben